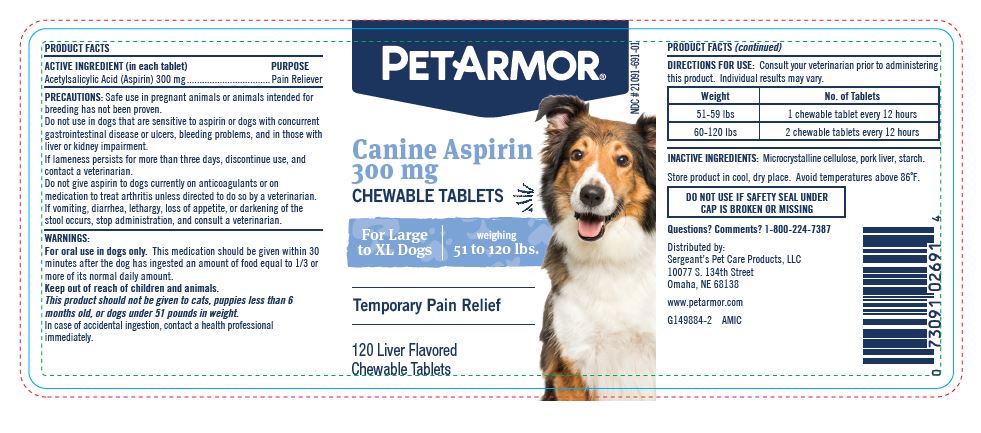 DRUG LABEL: Acetylsalicylic Acid
NDC: 21091-691 | Form: TABLET, CHEWABLE
Manufacturer: Sergeant's Pet Care Products LLC
Category: animal | Type: OTC ANIMAL DRUG LABEL
Date: 20230725

ACTIVE INGREDIENTS: ASPIRIN 300 mg/1 1
INACTIVE INGREDIENTS: MICROCRYSTALLINE CELLULOSE; PORK LIVER, COOKED; STARCH, CORN

PetArmor Canine Aspirin 300 mg

ACTIVE INGREDIENT (in each tablet)

Acetylsalicylic Acid (Aspirin) 300 mg

PRECAUTIONS:

Safe use in pregnant animals or animals intended for breeding has not been proven.

Do not use in dogs that are sensitive to aspirin or dogs with concurrent gastrointestinal disease or ulcers, bleeding problems, and in those with liver or kidney impairment.

If lameness persists for more than three days, discontinue use, and contact a veterinarian.

Do not give aspirin to dogs concurrently on anticoagulants or on medication to treat arthritis unless directed to do so by a veterinarian.

If vomiting, diarrhea, lethargy, loss of appetite, or darkening of the stool occurs, stop administration, and consult a veterinarian.

WARNINGS:

For oral use in dogs only. This medication should be given within 30 minutes after the dog has ingested an amount of food equal to 1/3 or more of its normal daily amount.

Keep out of reach of the children and animals.

This product should not be given to cats, puppies less than 6 months old, or dogs under 51 pounds in weight.

In case of accidental ingestion, contact a health professional immediately.

DIRECTIONS FOR USE:

Consult your veterinarian prior to administering this product. Individual results may vary.

Weight | No. of Tablets
51-59 lbs | 1 chewable tablet every 12 hours
60-120 lbs | 2 chewable tablets every 12 hours

INACTIVE INGREDIENTS:

Microcrystalline cellulose, pork liver, starch.

STORAGE AND HANDLING

Store product in cool, dry place. Avoid temperatures above 86°F.

DO NOT USE IF SAFETY SEAL UNDER

CAP IS BROKEN OR MISSING

Questions? Comments? 1-800-224-7387